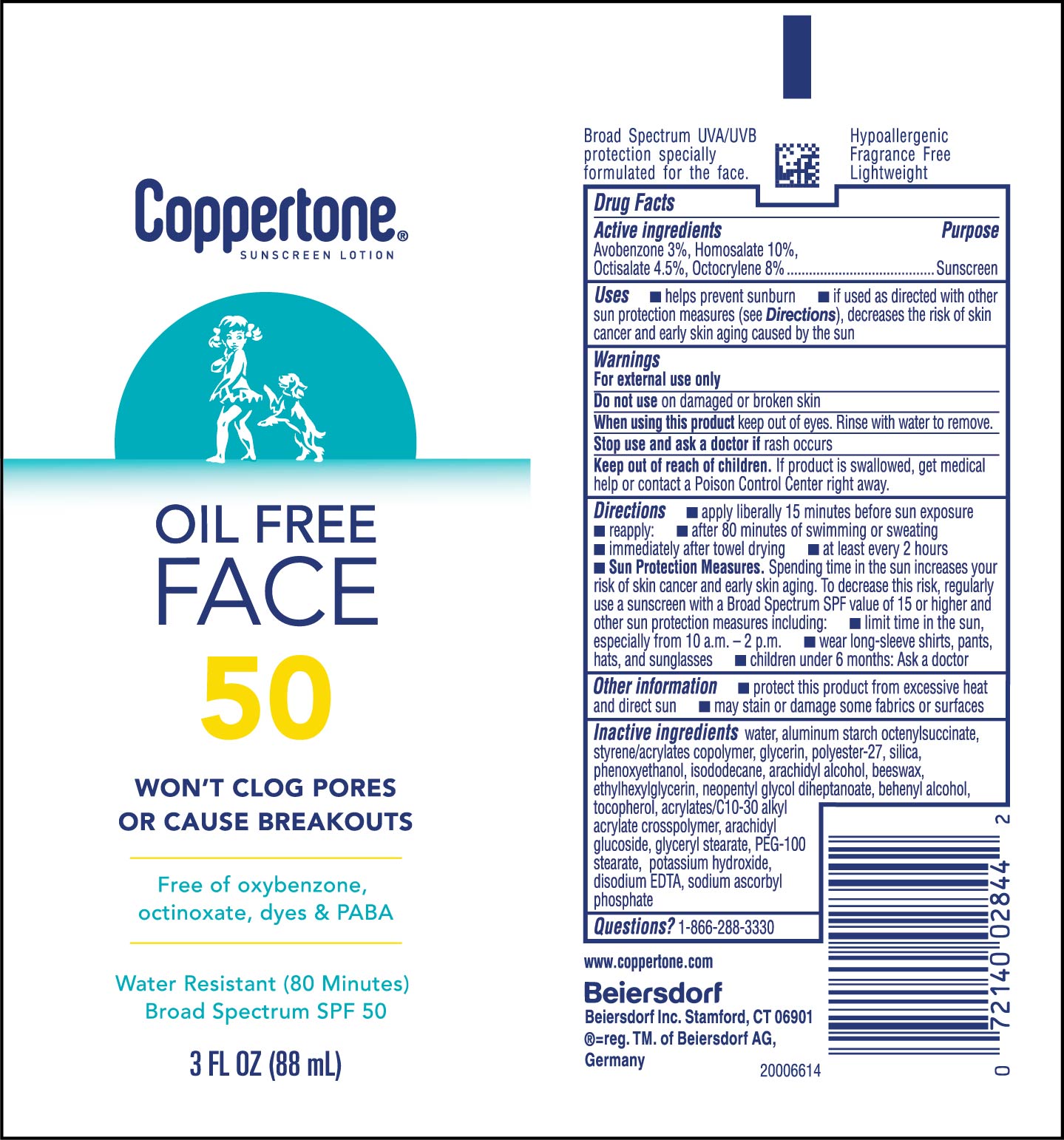 DRUG LABEL: Coppertone Oil Free SPF 50 Sunscreen
NDC: 66800-4094 | Form: LOTION
Manufacturer: Beiersdorf Inc
Category: otc | Type: HUMAN OTC DRUG LABEL
Date: 20251231

ACTIVE INGREDIENTS: OCTOCRYLENE 8 g/100 g; AVOBENZONE 3 g/100 g; OCTISALATE 4.5 g/100 g; HOMOSALATE 10 g/100 g
INACTIVE INGREDIENTS: WATER; POTASSIUM HYDROXIDE; ALUMINUM STARCH OCTENYLSUCCINATE; TOCOPHEROL; GLYCERYL STEARATE SE; PEG-100 STEARATE; DISODIUM EDTA-COPPER; SODIUM ASCORBYL PHOSPHATE; ARACHIDYL GLUCOSIDE; POLYESTER-7; ETHYLHEXYLGLYCERIN; GLYCERIN; PHENOXYETHANOL; ARACHIDYL ALCOHOL; STYRENE/ACRYLAMIDE COPOLYMER (MW 500000); SYNTHETIC BEESWAX; NEOPENTYL GLYCOL DIHEPTANOATE; DOCOSANOL; CARBOMER INTERPOLYMER TYPE A (55000 CPS); SILICON DIOXIDE; ISODODECANE

Oil Free Lotion SPF 50

Active ingredients

Avobenzone 3%, Homosalate 10%, Octisalate 4.5%, Octocrylene 8%

Purpose

Sunscreen

Uses

■ helps prevent sunburn

■ if used as directed with other sun protection measures (see Directions), decreases the risk of skin cancer and early skin aging caused by the sun

Warnings

For external use only

Do not useon damaged or broken skin

WHEN USING

When using this productkeep out of eyes. Rinse with water to remove.

Stop use and ask a doctor ifrash occurs

Keep out of reach of children.If product is swallowed, get medical help or contact a Poison Control Center right away.

Directions

■ apply liberally 15 minutes before sun exposure

■ reapply:

■ after 80 minutes of swimming or sweating

■ immediately after towel drying

■ at least every 2 hours

■ Sun Protection Measures.Spending time in the sun increases your risk of skin cancer and early skin aging. To decrease this risk, regularly use a sunscreen with a Broad Spectrum SPF value of 15 or higher and other sun protection measures including:

■ limit time in the sun, especially from 10 a.m. – 2 p.m.

■ wear long-sleeve shirts, pants, hats, and sunglasses

■ children under 6 months: Ask a doctor

Other information

■ protect this product from excessive heat and direct sun

■ may stain or damage some fabrics or surfaces

Inactive ingredients

water, aluminum starch octenylsuccinate, styrene/acrylates copolymer, glycerin, polyester-27, silica, phenoxyethanol, isododecane, arachidyl alcohol, beeswax, ethylhexylglycerin, neopentyl glycol diheptanoate, behenyl alcohol, tocopherol, acrylates/C10-30 alkyl acrylate crosspolymer, arachidyl glucoside, glyceryl stearate, PEG-100 stearate, potassium hydroxide, disodium EDTA, sodium ascorbyl phosphate

Questions?

1-866-288-3330

PACKAGE LABEL

Coppertone® Sunscreen Lotion

Oil Free FACE

50

Won't clog pores or cause breaksouts

Free of oxybenzone, octinoxate, dyes & PABA

Water Resistant (80 Minutes)

Broad Spectrum SPF 50

3 FL OZ (88 mL)